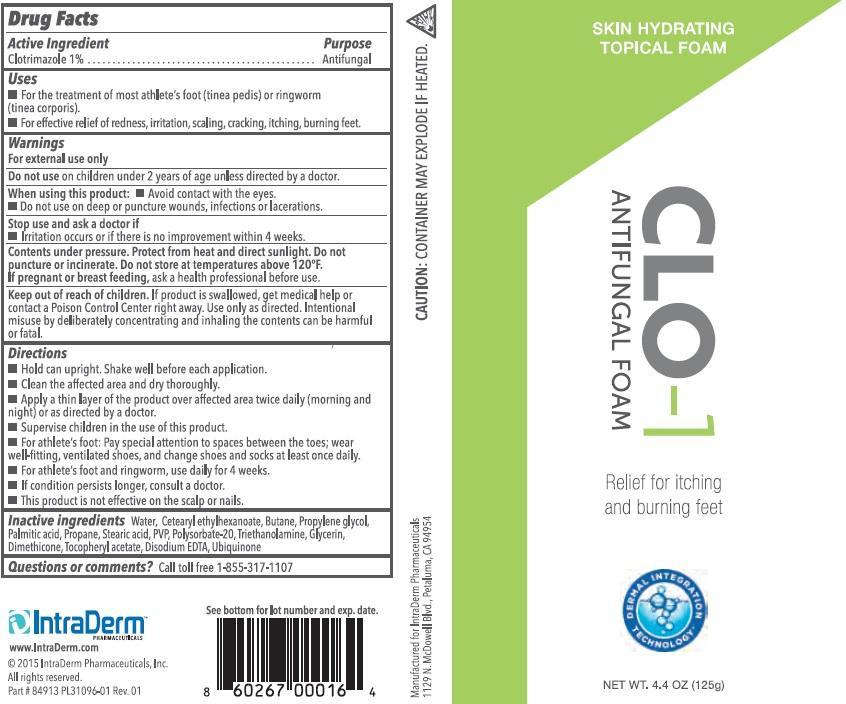 DRUG LABEL: Occulus
NDC: 13630-0092 | Form: AEROSOL, FOAM
Manufacturer: Prime Packaging, Inc.
Category: otc | Type: HUMAN OTC DRUG LABEL
Date: 20200117

ACTIVE INGREDIENTS: CLOTRIMAZOLE 10 mg/1 g
INACTIVE INGREDIENTS: CETEARYL ETHYLHEXANOATE; DIMETHICONE; EDETATE DISODIUM; GLYCERIN; PALMITIC ACID; POLYSORBATE 20; PROPYLENE GLYCOL; POVIDONE, UNSPECIFIED; STEARIC ACID; .ALPHA.-TOCOPHEROL ACETATE; TROLAMINE; UBIDECARENONE; WATER

Active ingredient

Clotrimazole 1%

Purpose

Antifungal

Uses

- For the treatment of most athlete's foot (tinea pedis) or ringworm (tinea corporis).
- For effective relief of redness, irritation, scaling, cracking, itching, burning feet.

Warnings

OTHER SAFETY INFORMATION

For external use only

Do not use on children under 2 years of age unless directed by a doctor.

When using this product: • Avoid contact with the eyes. • Do not use on deep or puncture wounds, infections or lacerations.

Stop use and ask a doctor if

- Irritation occurs or if there is no improvement within 4 weeks.

Contents under pressure. Protect from heat and direct sunlight. Do not puncture or incinerate. Do not store at temperatures above 120°F. If pregnant or breast feeding, ask a health professional before use.

Keep out of reach of children. If product is swallowed, get medical help or contact a Poison Control Center right away. Use only as directed. Intentional misuse by deliberately concentrating and inhaling the contents can be harmful or fatal.

Directions

- Hold can upright. Shake well before each application.
- Clean the affected area and dry thoroughly.
- Apply a thin layer of the product over affected area twice daily (morning and night) or as directed by a doctor.
- Supervise children in the use of this product.
- For athlete's foot: Pay special attention to spaces between the toes; wear well-fitting, ventilated shoes, and change shoes and socks at least once daily.
- For athlete's foot and ringworm, use daily for 4 weeks.
- If condition persists longer, consult a doctor.
- This product is not effective on the scalp or nails.

Inactive Ingredients

Water, Cetearyl ethylhexanoate, Butane, Propylene glycol, Palmitic acid, Propane, Stearic Acid, PVP, Polysorbate-20, Triethanolamine, Glycerin, Dimethicone, Tocopheryl Acetate, Disodium EDTA, Ubiquinone

Questions or comments? Call toll free 1-855-317-1107

PRINCIPAL DISPLAY PANEL - 125 g Can Label

SKIN HYDRATING

TOPICAL FOAM

CLO-1

ANTIFUNGAL FOAM

Relief for itching

and burning feet

NET WT. 4.4 OZ (125g)